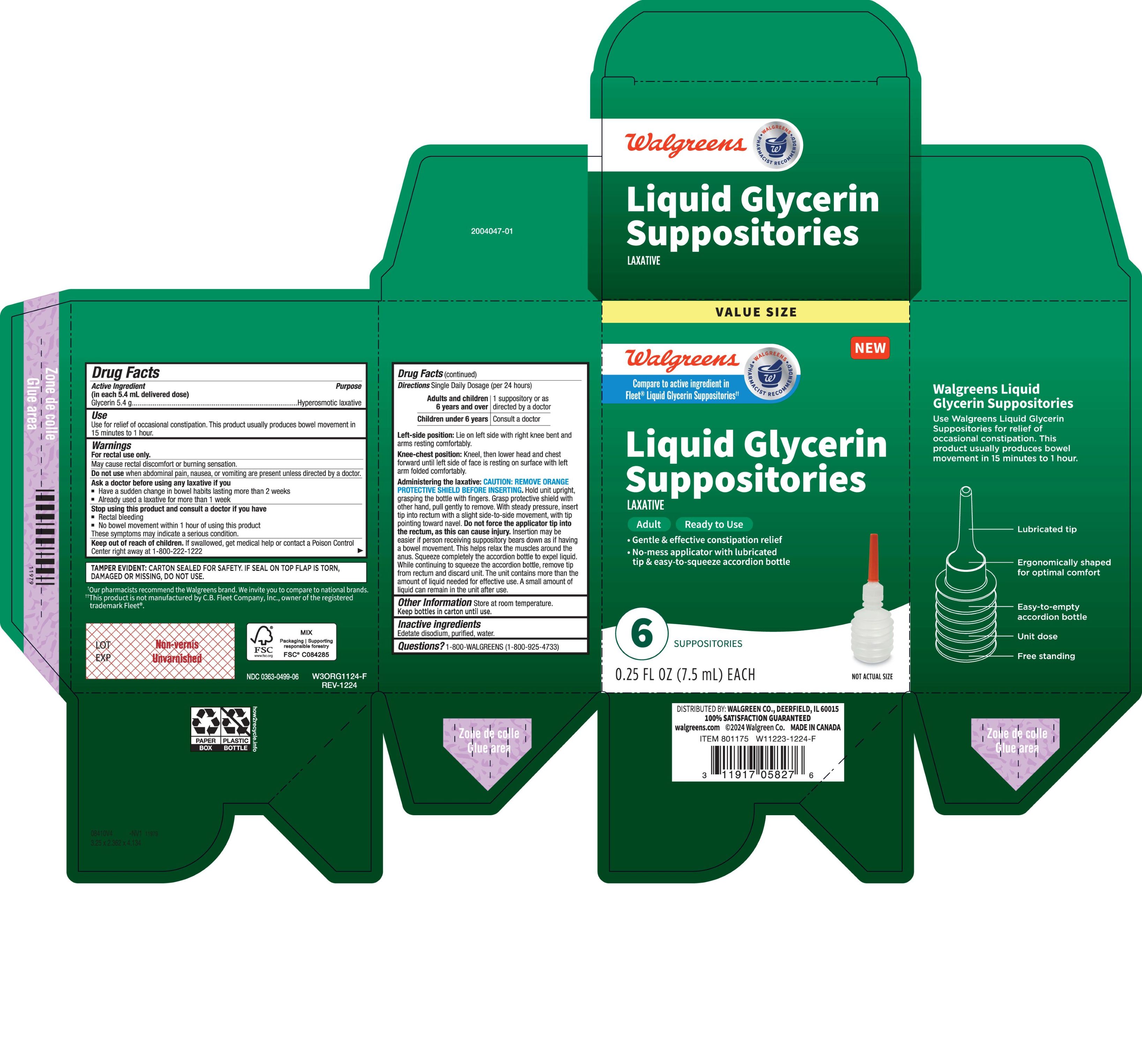 DRUG LABEL: WALGREENS GLYCERIN
NDC: 0363-0499 | Form: ENEMA
Manufacturer: Walgreens
Category: otc | Type: HUMAN OTC DRUG LABEL
Date: 20250220

ACTIVE INGREDIENTS: GLYCERIN 5.4 g/1 1
INACTIVE INGREDIENTS: EDETATE DISODIUM

WALG GLYCERIN APPLICATR 7.5ML 6S

PURPOSE

Hyperosmotic Laxative

INDICATIONS AND USAGE

for relief of occasional constipation.
This product usually produces a bowel movement in 15 minutes to 1 hour.

WARNINGS

May cause rectal discomfort or a burning sensation.
For rectal use only

Do not use when abdominal pain, nausea, or vomiting are present unless directed by a doctor.

Ask a doctor before using any laxative if you

- have a sudden change in bowel habits lasting more than 2 weeks
- already used a laxative for more than 1 week

STOP USE

Stop using this product and consult a doctor if you have

- rectal bleeding
- no bowel movement within 1 hour of using this product

These symptoms may indicate a serious condition.

KEEP OUT OF REACH OF CHILDREN

If swallowed, get medical help or contact a Poison Control Center right away at 1-800-222-1222

Single Daily Dosage (per 24 hours)

- Adults and children 6 years and over: 1 suppository or as directed by a doctor
- Children under 6 years: consult a doctor

Left-side position: Lie on left side with right knee bent and arms resting comfortably.

Knee-chest position: Kneel, then lower head and chest forward until left side of face is resting on surface with left arm folded comfortably.

Administering the laxative:

CAUTION: REMOVE ORANGE PROTECTIVE SHIELD BEFORE INSERTING.

Hold unit upright, grasping the bottle with fingers. Grasp protective shield with other hand, pull gently to remove. With steady pressure, insert tip into rectum with a slight side-to-side movement, with tip pointing toward navel. Do not force the applicator tip into the rectum, as this can cause injury. Insertion may be easier if person receiving suppository bears down as if having a bowel movement. This helps relax the muscles around the anus. Squeeze completely the accordion bottle to expel liquid. While continuing to squeeze the accordion bottle, remove tip from rectum and discard unit. The unit contains more than the amount of liquid needed for effective use. A small amount of liquid will remain in the unit after use.

INACTIVE INGREDIENT

edetate disodium, purified water

STORAGE AND HANDLING

Store at room temperature.

Keep bottles in carton until use.

Questions? 1-800-WALGREENS (1-800-925-4733)